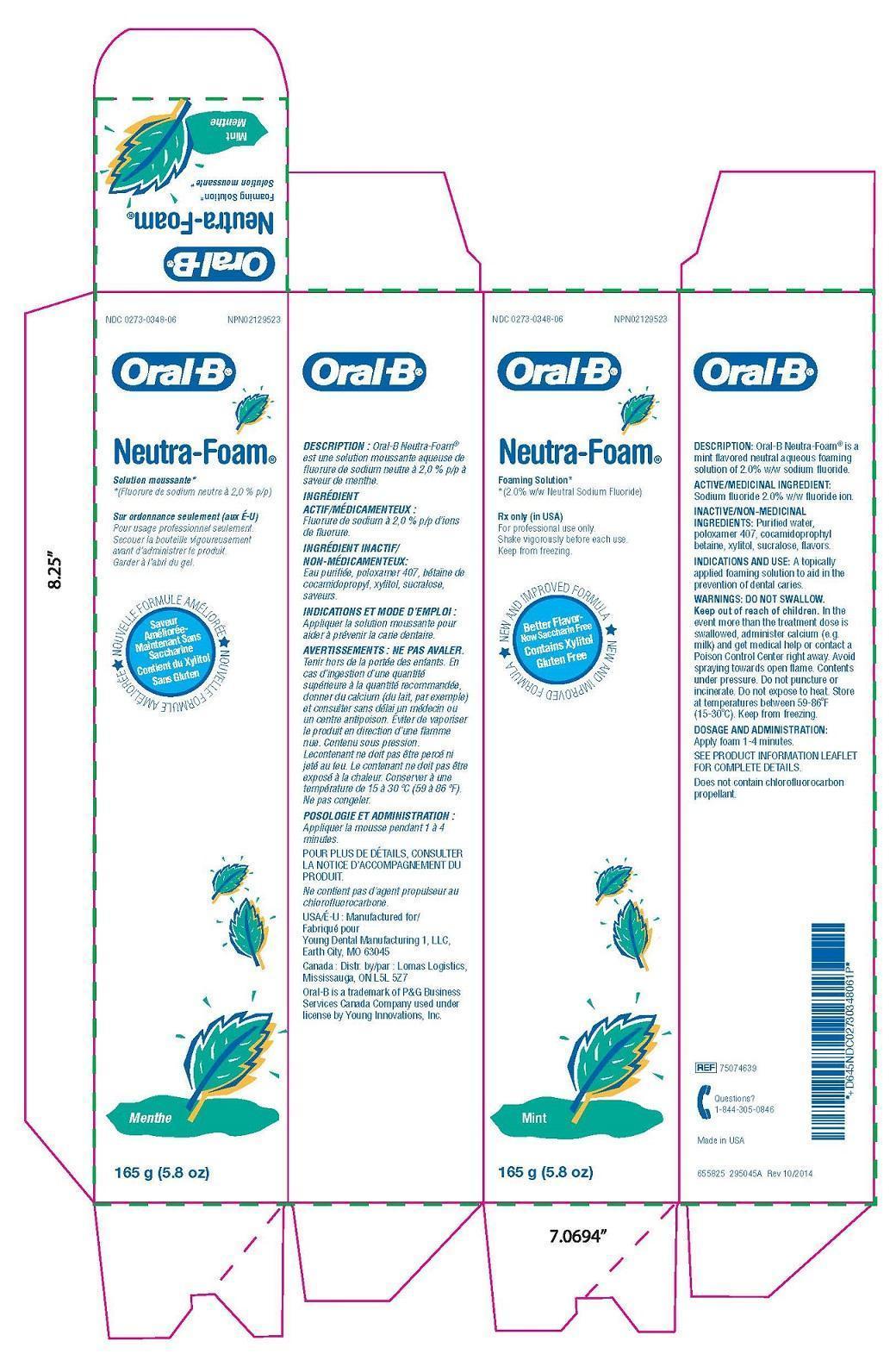 DRUG LABEL: Oral B  Neutra Foam

NDC: 0273-0348 | Form: SOLUTION
Manufacturer: YOUNG DENTAL MANUFACTURING CO 1, LLC
Category: prescription | Type: HUMAN PRESCRIPTION DRUG LABEL
Date: 20230113

ACTIVE INGREDIENTS: SODIUM FLUORIDE 0.5 mg/1 g
INACTIVE INGREDIENTS: WATER; COCAMIDOPROPYL BETAINE; POLOXAMER 407; XYLITOL; SUCRALOSE

Oral B Neutra Foam

Descrption

Oral-B Neutra-Foam ® is a mint flavored neutral aqueous foaming solution of 2.0% w/w sodium fluoride.

Inactives

Purified water,poloxamer 407, cocamidoprophylbetaine, xylitol, sucralose, flavors.

Indication and Usage

A topically applied foaming solution to aid in the prevention of dental caries.

Warnings

In theevent more than the treatment dose isswallowed, administer calcium (e.g.milk) and get medical help or contact aPoison Control Center right away. Avoidspraying towards open flame. Contentsunder pressure. Do not puncture orincinerate. Do not expose to heat. Storeat temperatures between 59-86°F(15-30°C). Keep from freezing.

Package Label

Product Label